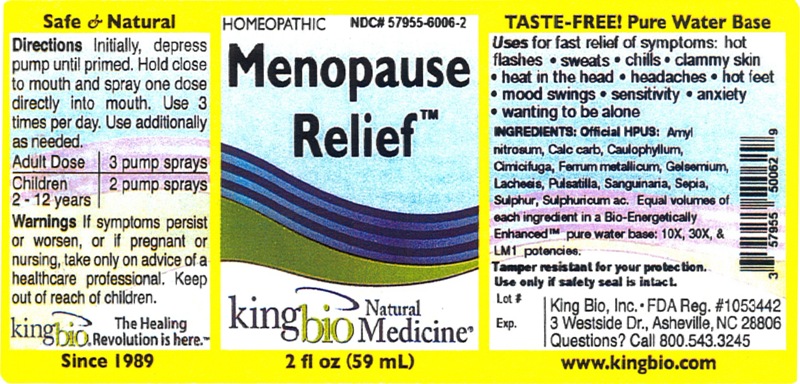 DRUG LABEL: Menopause Relief
NDC: 57955-6006 | Form: SPRAY
Manufacturer: King Bio Inc
Category: homeopathic | Type: HUMAN OTC DRUG LABEL
Date: 20120307

ACTIVE INGREDIENTS: AMYL NITRITE 10 [hp_X]/59 mL; OYSTER SHELL CALCIUM CARBONATE, CRUDE 10 [hp_X]/59 mL; CAULOPHYLLUM THALICTROIDES ROOT 10 [hp_X]/59 mL; BLACK COHOSH 10 [hp_X]/59 mL; IRON 10 [hp_X]/59 mL; GELSEMIUM SEMPERVIRENS ROOT 10 [hp_X]/59 mL; LACHESIS MUTA VENOM 10 [hp_X]/59 mL; PULSATILLA VULGARIS 10 [hp_X]/59 mL; SANGUINARIA CANADENSIS ROOT 10 [hp_X]/59 mL; SEPIA OFFICINALIS JUICE 10 [hp_X]/59 mL; SULFUR 10 [hp_X]/59 mL; SULFURIC ACID 10 [hp_X]/59 mL
INACTIVE INGREDIENTS: WATER

Menopause Relief

Active Ingredients

Official HPUS: Amyl nitrosum, Calcarea carbonica, Caulophyllum thalictroides, Cimicifuga racemosa, Ferrum metallicum, Gelsemium sempervirens, Lachesis mutus, Pulsatilla, Sanguinaria canadensis, Sepia, Sulphur, Sulphuricum acidum.

Reference image menopauserelief.jpg

Purpose

for fast relief of symptoms:

- hot flashes
- sweats
- chills
- clammy skin
- heat in the head
- headaches
- hot feet
- mood swings
- sensitivity
- anxiety
- wanting to be alone

Reference image menopauserelief.jpg

Inactive Ingredient

Equal volumes of each ingredient in a Bio-Energetically Enhanced pure water base: 10X, 30X, and LM1 potencies.

Reference image menopauserelief.jpg

Warnings

If symptoms persist or worsen, or if pregnant or nursing, take only on advice of a healthcare professional. Keep out of reach of children.

Other: Tamper resistant for your protection. Use only if safety seal is intact.

Reference image menopauserelief.jpg

Indications and Usage

For fast relief of symptoms: hot flashes, sweats, chills, clammy skin, heat in the head, headaches, hot feet, mood swings, sensitivity, anxiety, wanting to be alone.

Reference image menopauserelief.jpg

Keep Out of Reach of Children

Warning: Keep out of reach of children.

Reference image menopauserelief.jpg

Dosage and Administration

Directions: Initially, depress pump until primed. Hold close to mouth and spray one dose directly into mouth. Use 3 times per day. Use additionally as needed.

Adult Dose - 3 Pump Sprays

Children (2-12 Years) - 2 Pump Sprays

Reference image menopauserelief.jpg

PACKAGE LABEL

King Bio Inc.

3 Westside Drive

Asheville, NC 28806

Questions? Call 800.543.3245

www.kingbio.com

reference image menopauserelief.jpg